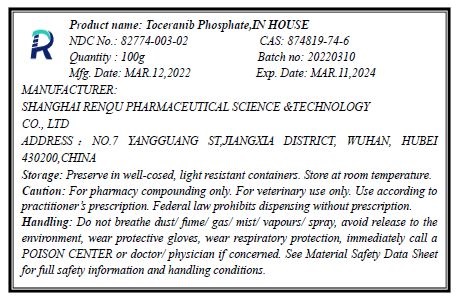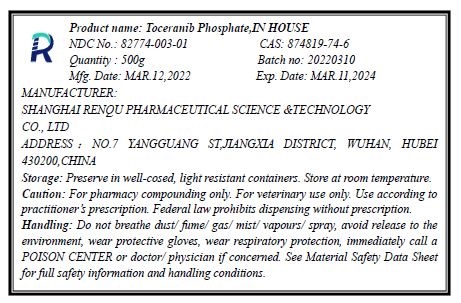 DRUG LABEL: Toceranib Phosphate
NDC: 82774-003 | Form: POWDER
Manufacturer: Shanghai Renqu Pharmaceutical Science & Technology Co., Ltd.
Category: other | Type: BULK INGREDIENT - ANIMAL DRUG
Date: 20220621

ACTIVE INGREDIENTS: TOCERANIB PHOSPHATE 1 g/1 g

Toceranib Phosphate